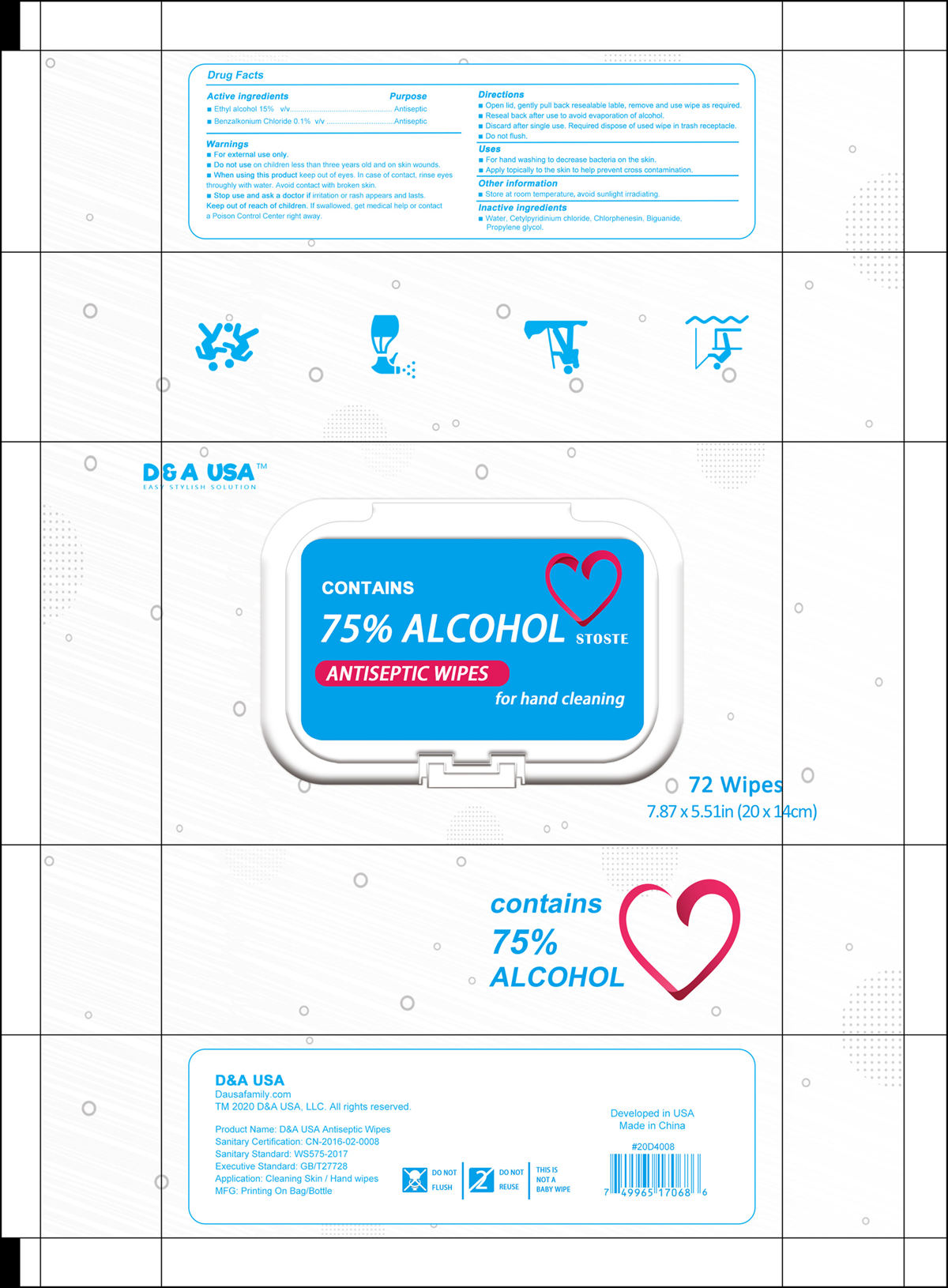 DRUG LABEL: Antiseptic Wipes
NDC: 79288-013 | Form: CLOTH
Manufacturer: Xiamen Yiukin Paper Products Co.,ltd
Category: otc | Type: HUMAN OTC DRUG LABEL
Date: 20211231

ACTIVE INGREDIENTS: ALCOHOL 15 mL/100 g; BENZALKONIUM CHLORIDE 0.1 g/100 g
INACTIVE INGREDIENTS: BIGUANIDE; PROPYLENE GLYCOL; WATER; CETYLPYRIDINIUM CHLORIDE; CHLORPHENESIN

Antiseptic Wipes

Active Ingredients

Ethyl alcohol 15%. Purpose: Antiseptic

Benzalkonium Chloride 0.1%. Purpose: Antiseptic

Purpose

Antiseptic

Warnings

- For external use only.

Do not use

on children less than three years old and on skin wounds.

When using this product

Keep out of eyes. In case of contact, rinse eyes thoroughly with water. Avoid contact with broken skin.

Stop use and ask a doctor if

irritation or rash appears and lasts

Keep out of reach of children

If swallowed, get medical help or contact a Poison Control Center right away.

Directions

- Open lid, gently pull back resealable label, remove and use wipe as required.
- Reseal back after use to avoid evaporation of alcohol.
- Discard after single use Required dispose of used wipe in trash receptable.
- Do not flush

Uses

- For hand washIng to decrease bacteria on the skin.
- Apply topically to the skin to help prevent cross contamination.

Other information

Store at room temperature, avoid sunlight irradiating.

Inactive ingredients

Water, Cetylpyridinium chloride, Chlorphenesin, Biguanide, Propylene glycol

Package Label - Principal Display Panel

72 PCS NDC: 79288-013-01

D&A USA

CONTAINS

75% ALCOHOL STOSTE

ANTISEPTIC WIPES

for hand cleaning

72 Wipes

7.87 x 5.51 in (20 x 14 cm)